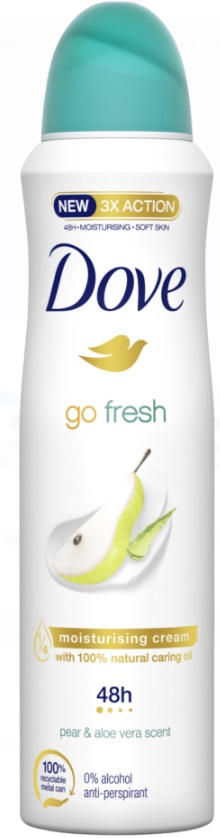 DRUG LABEL: Dove
NDC: 51769-088 | Form: AEROSOL, SPRAY
Manufacturer: All Natural Dynamics
Category: otc | Type: HUMAN OTC DRUG LABEL
Date: 20220317

ACTIVE INGREDIENTS: ALUMINUM CHLOROHYDRATE 20.2 g/100 g
INACTIVE INGREDIENTS: POLYETHYLENE GLYCOL 200; BENZYL ALCOHOL; BENZYL SALICYLATE; BUTANE; BUTYLPHENYL METHYLPROPIONAL; ISOBUTANE; .BETA.-CITRONELLOL, (R)-; PROPANE; LINALOOL, (+/-)-; CYCLOMETHICONE 5; PPG-14 BUTYL ETHER; SUNFLOWER OIL; ALKYL (C12-15) BENZOATE; DISTEARDIMONIUM HECTORITE; CYCLOMETHICONE; OCTYLDODECANOL; BUTYLATED HYDROXYTOLUENE; DIMETHICONOL (40 CST)

Go Fresh Pear and Aloe Vera Antiperspirant Deodorant

Go Fresh Pear and Aloe Vera Antiperspirant Deodorant- aluminum chlorohydrate aerosol, spray

Dove Pear & Aloe Vera 48hr protection

Drug Facts

Active ingredient

Aluminum Chlorohydrate (20.2%)

Purpose

antiperspirant

Uses

reduces underarm wetness

Warnings

• FLAMMABLE. DO NOT USE NEAR HEAT, FLAME, OR WHILE SMOKING. CAN CAUSE SERIOUS INJURY OR DEATH
• Keep away from face and mouth to avoid breathing in.
• Avoid spraying in eyes. Contents under pressure. Do not puncture or incinerate. Do not expose to heat or store at temperatures above 120°F/50°C or in enclosed places that could overheat
• Do not use on broken skin. Stop use if rash or irritation occurs.
• Ask a doctor before using if you have kidney disease.
• USE ONLY AS DIRECTED. INTENTIONAL MISUSE BY DELIBERATELY CONCENTRATING AND INHALING THE CONTENTS CAN BE HARMFUL OR FATAL.
Help stop inhalation abuse. For information visit www.inhalant.org

• KEEP OUT OF REACH OF CHILDREN

Directions

apply to underarms only

Inactive ingredients

Butane, Isobutane, Propane, Aluminum Chlorohydrate, Cyclopentasiloxane, PPG-14 Butyl Ether, Parfum, Helianthus Annuus Seed Oil, C12-15 Alkyl Benzoate, Disteardimonium Hectorite, Octyldodecanol, BHT, Dimethiconol, Propylene Carbonate, PEG-4, Benzyl Alcohol, Benzyl Salicylate, Butylphenyl Methylpropional, Citronellol, Linalool.

Questions?

Call toll-free 1-800-761-3683